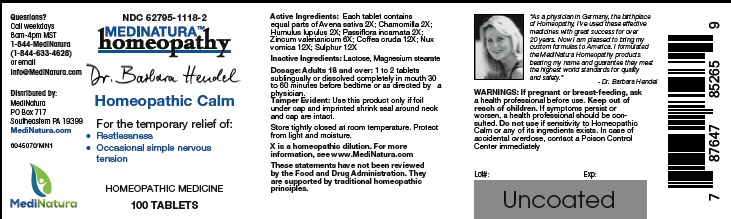 DRUG LABEL: Hendel Homeopathic Calm
NDC: 62795-1118 | Form: TABLET
Manufacturer: MediNatura Inc
Category: homeopathic | Type: HUMAN OTC DRUG LABEL
Date: 20220822

ACTIVE INGREDIENTS: AVENA SATIVA FLOWERING TOP 2 [hp_X]/1 1; MATRICARIA CHAMOMILLA 2 [hp_X]/1 1; HOPS 2 [hp_X]/1 1; PASSIFLORA INCARNATA FLOWERING TOP 2 [hp_X]/1 1; ZINC VALERATE DIHYDRATE 6 [hp_X]/1 1; ARABICA COFFEE BEAN 12 [hp_X]/1 1; STRYCHNOS NUX-VOMICA SEED 12 [hp_X]/1 1; SULFUR 12 [hp_X]/1 1
INACTIVE INGREDIENTS: LACTOSE MONOHYDRATE; MAGNESIUM STEARATE

Hendel Homeopathic Calm

WARNINGS

If pregnant or breast-feeding, ask a health professional before use. Keep out of reach of children. If symptoms persist or worsen, a health professional should be consulted. Do not use if sensitivity to Homeopathic Calm or any of its ingredients exists. In case of accidental overdose, contact a Poison Control Center immediately

KEEP OUT OF REACH OF CHILDREN

INDICATIONS

Restlessness Occasional and simple nervous tension

ACTIVE INGREDIENTS

Each tablet contains equal parts of Avena sativa 2X; Chamomilla 2X; Humulus lupulus 2X; Passiflora incarnata 2X; Zincum valerianicum 6X; Coffea cruda 12X; Nux vomica 12X; Sulphur 12X

INACTIVE INGREDIENT

Lactose, Magnesium stearate

DOSAGE

Adults 18 and over: 1 to 2 tablets sublingually or dissolved completely in mouth 30 to 60 minutes before bedtime or as directed by a physician.

USES

For the temporary relief of:
• Restlessness
• Occasional simple nervous tension

PACKAGE LABEL

Add image transcription here...